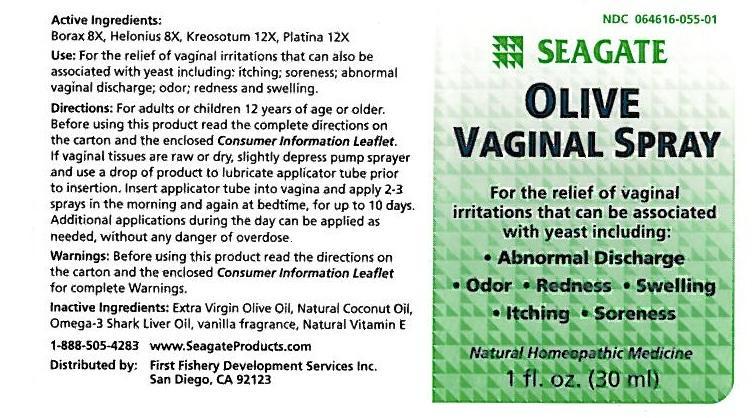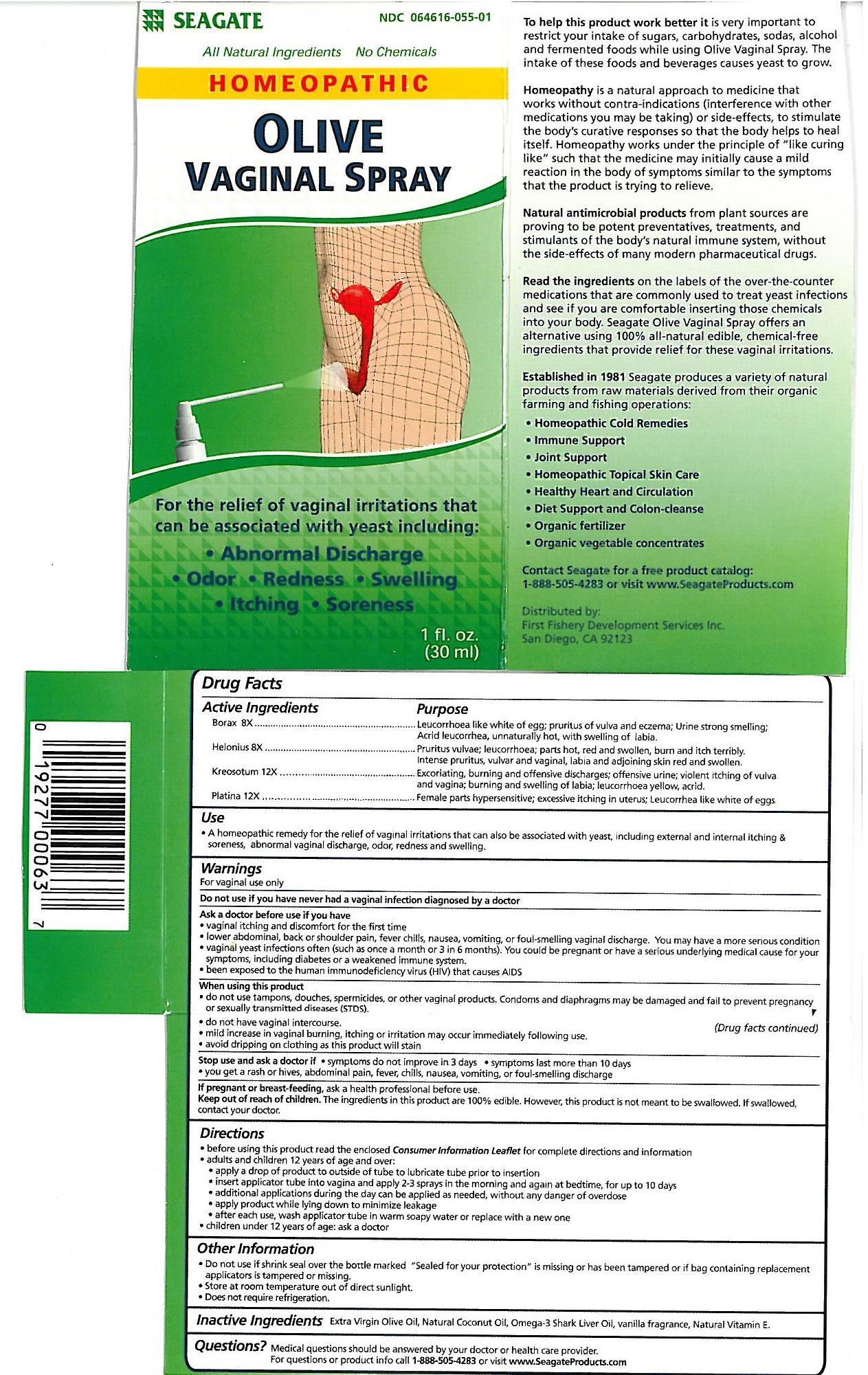 DRUG LABEL: Olive Vaginal Formula
NDC: 64616-055 | Form: SPRAY
Manufacturer: Vitality Works, Inc
Category: homeopathic | Type: HUMAN OTC DRUG LABEL
Date: 20251217

ACTIVE INGREDIENTS: SODIUM BORATE 8 [hp_X]/1 mL; CHAMAELIRIUM LUTEUM ROOT 8 [hp_X]/1 mL; WOOD CREOSOTE 12 [hp_X]/1 mL; PLATINUM 12 [hp_X]/1 mL
INACTIVE INGREDIENTS: OLIVE OIL; COCONUT OIL; SHARK LIVER OIL; ALPHA-TOCOPHEROL; VANILLA

Olive Vaginal Spray

Olive Vaginal Spray

Borax 8X

Helonius 8X

Kreosotum 12X

Platina 12X

Olive Vaginal Spray

Extra Virgin Olive Oil, Natural Coconut Oil, Omega-3 Shark Liver Oil, vanilla fragrance, Natural Vitamin E

Olive Vaginal Spray

Do not use if have never had a vaginal infection diagnosed by a doctor.

Ask a doctor before use if you have:

-vaginal itching and discomfort for the first time.

-lower abdomina, back or shoulder pain, fever chills, nausea, vomiting or foul-smelling vaginal discharge. You may have a more serious condition

-vaginal yeast infections ofter (such as once a month or 3 in 6 months). You could be pregnant or have a serious underlying medical cause for your syptoms, including diabetes or a weakened immune system.

-been exposed to the human immunodeficiency virus (HIV) that causes AIDS.

Olive Vaginal Spray

Keep out of reach of children. The ingredients in this product are 100% edible. However, this product is not meant to be swallowed. If swallowed, contact you doctor.

Olive Vaginal Spray

A homeopathic remedy for the relief of vaginal irritations that can also be associatied with yeast, including external and internal itching & soreness, abnormal vaginal discharge, odor, redness and swelling.

Olive Vaginal Spray

Adults and children 12 years of age and over:

-Apply a drop of product to outside of tube to lubricate tube prior to insertion.

-Insert applicator tube into vagina and apply 2-3 sprays in the morning and again at bedtime, for up to 10 days.

-additional applications during the day can be applied as needed without any danger of overdose.

-apply product while lying down to minimize leakage.

-after each use, wash applicator tube in warm soapy water or replace with a new one.

Children under 12 years of age, ask a doctor.

Olive Vaginal Spray

Borax - Leucorrhoea like white of egg; pruritius of vulva and eczema; Urine strong smelling; Acrid leucorrhea, unnaturally hot with swelling of labia.

Helonius - Pruritus vulvae; leucorrhoea; parts hot, red and swollen, burn and itch terribly. Intense pruritus, vulvar and vaginal, labia and adjoining skin red and swollen.

Kreosotum - Excoriating, buring and offensive discharges; offensive urine; violent itching of vulva and vagina; burnign and welling of labia; leucorrhoea yellow, acrid.

Platina - Female parts hypersensitive; excessive itching in uterus; Leucorrhea like white of eggs.